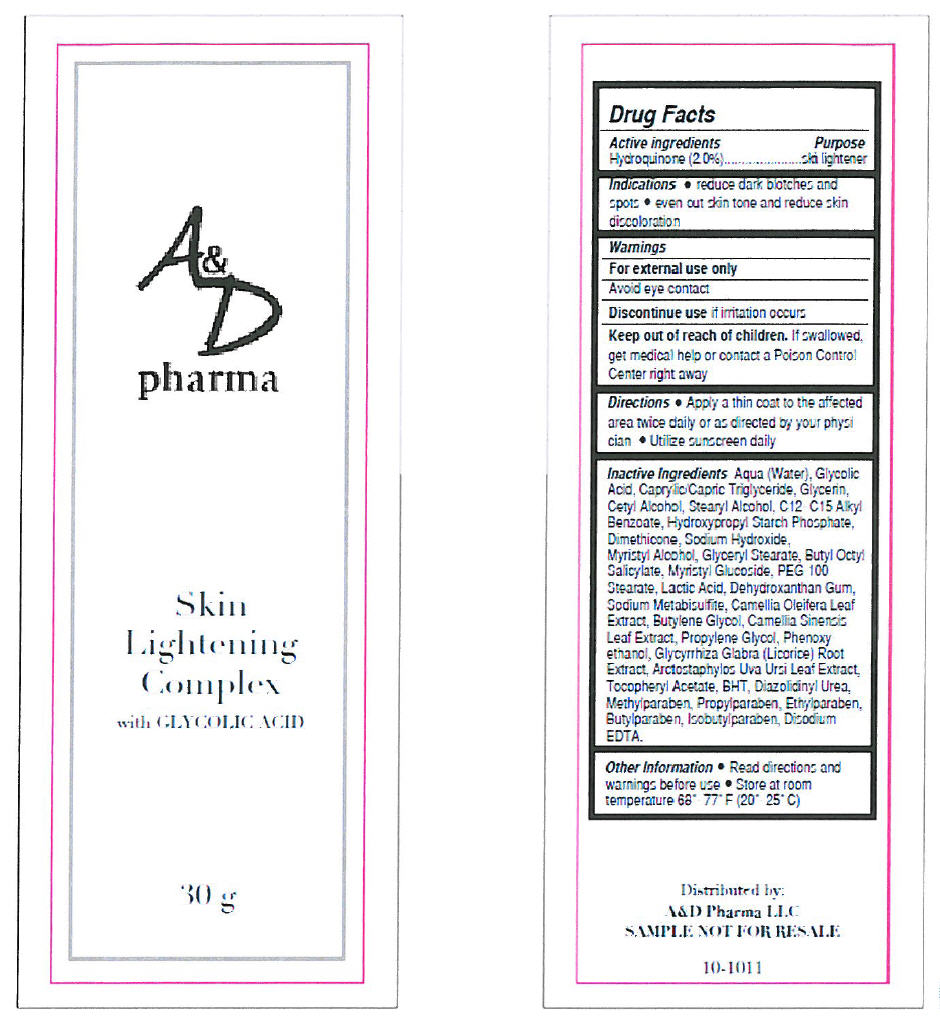 DRUG LABEL: SKIN LIGHTENING COMPLEX
NDC: 65113-8401 | Form: CREAM
Manufacturer: G.S. COSMECEUTICAL USA, INC.
Category: otc | Type: HUMAN OTC DRUG LABEL
Date: 20100902

ACTIVE INGREDIENTS: HYDROQUINONE 2 g/100 g
INACTIVE INGREDIENTS: Water; Glycolic Acid; Medium-Chain Triglycerides; Glycerin; Cetyl Alcohol; Stearyl Alcohol; C12-15 Alkyl Benzoate; Dimethicone; Sodium Hydroxide; Myristyl Alcohol; Glyceryl Monostearate; Polyoxyl 100 Stearate; Lactic Acid; Sodium Metabisulfite; Butylene Glycol; Green Tea Leaf; Propylene Glycol; Phenoxyethanol; Glycyrrhiza Glabra; Arctostaphylos Uva-Ursi Leaf; Alpha-Tocopherol Acetate; Butylated Hydroxytoluene; Diazolidinyl Urea; Methylparaben; Propylparaben; Ethylparaben; Butylparaben; Isobutylparaben; Edetate Disodium

A&D pharma
Skin
Lightening
Complex
with GLYCOLIC ACID

Drug Facts

Active ingredients

Hydroquinone (2.0%)

Purpose

skin lightener

Indications

- reduce dark blotches and spots
- even out skin tone and reduce skin discoloration

Warnings

For external use only

WHEN USING

Avoid eye contact

Discontinue use if irritation occurs

Keep out of reach of children. If swallowed, get medical help or contact a Poison Control Center right away

Directions

- Apply a thin coat to the affected area twice daily or as directed by your physician
- Utilize sunscreen daily

Inactive Ingredients

Aqua (Water), Glycolic Acid, Caprylic/Capric Triglyceride, Glycerin, Cetyl Alcohol, Stearyl Alcohol, C12-C15 Alkyl Benzoate, Hydroxypropyl Starch Phosphate, Dimethicone, Sodium Hydroxide, Myristyl Alcohol, Glyceryl Stearate, Butyl Octyl Salicylate, Myristyl Glucoside, PEG 100 Stearate, Lactic Acid, Dehydroxanthan Gum, Sodium Metabisulfite, Camellia Oleifera Leaf Extract, Butylene Glycol, Camellia Sinensis Leaf Extract, Propylene Glycol, Phenoxy ethanol, Glycyrrhiza Glabra (Licorice) Root Extract, Arctostaphylos Uva Ursi Leaf Extract, Tocopheryl Acetate, BHT, Diazolidinyl Urea, Methylparaben, Propylparaben, Ethylparaben, Butylparaben, Isobutylparaben, Disodium EDTA.

Other Information

- Read directions and warnings before use
- Store at room temperature 68°-77° F (20°-25° C)

Distributed by:
A&D Pharma LLC

PRINCIPAL DISPLAY PANEL - 30 g Tube Label

A&D
pharma

Skin
Lightening
Complex
with GLYCOLIC ACID

30 g